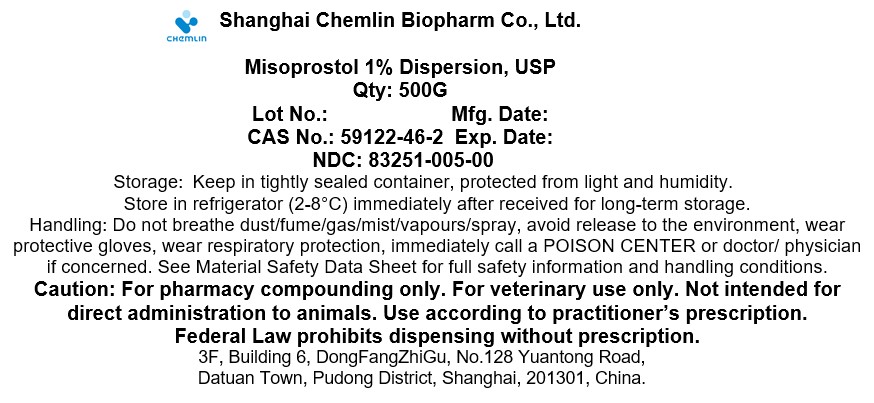 DRUG LABEL: Misoprostol 1% Dispersion
NDC: 83251-005 | Form: POWDER
Manufacturer: Shanghai Chemlin Biopharm Co., Ltd.
Category: other | Type: BULK INGREDIENT - ANIMAL DRUG
Date: 20241003

ACTIVE INGREDIENTS: Misoprostol 0.01 g/1 g
INACTIVE INGREDIENTS: HYPROMELLOSE, UNSPECIFIED 0.99 g/1 g

Misoprostol 1% Dispersion